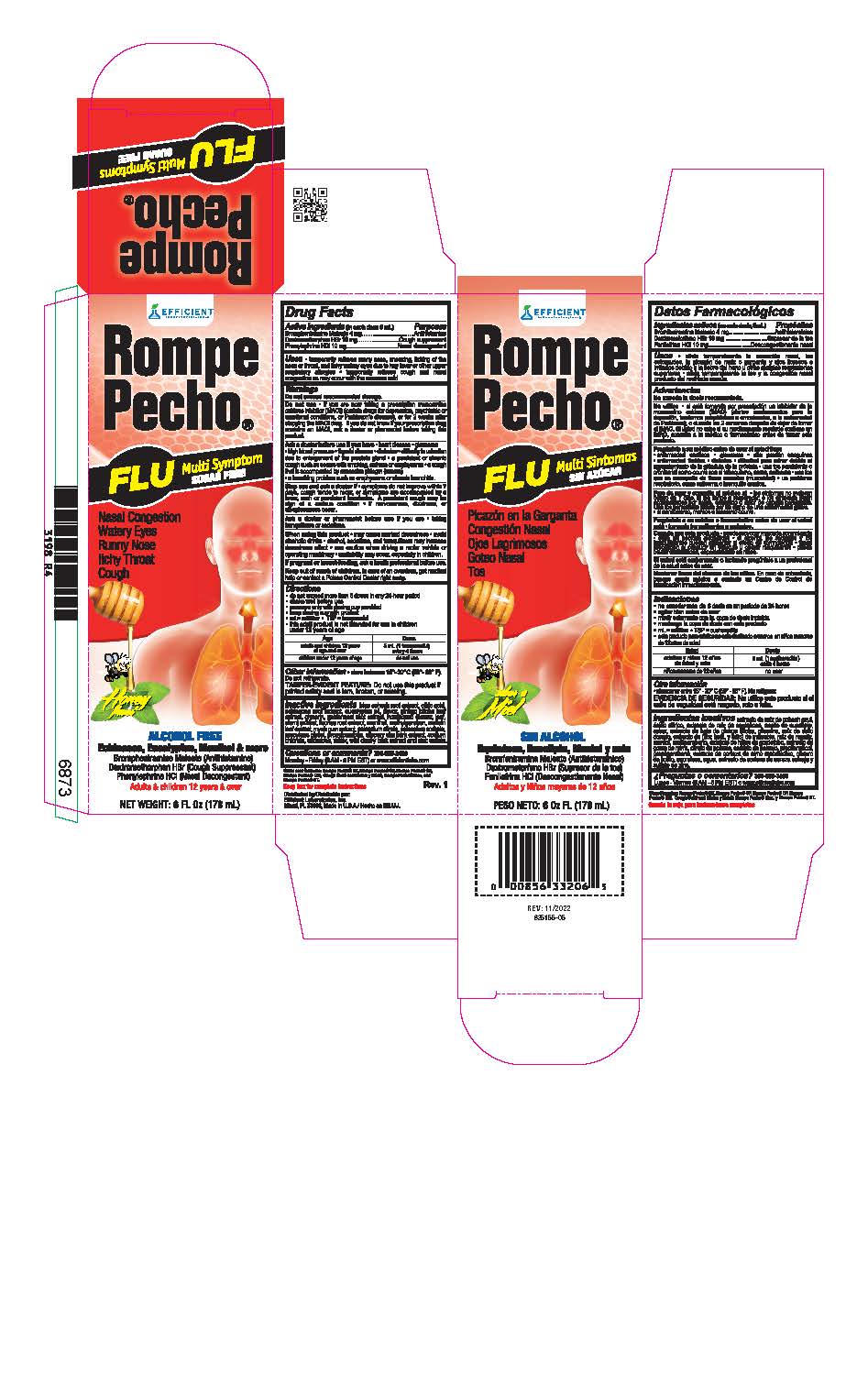 DRUG LABEL: Rompe Pecho
NDC: 58593-225 | Form: LIQUID
Manufacturer: Efficient Laboratories Inc
Category: otc | Type: HUMAN OTC DRUG LABEL
Date: 20250326

ACTIVE INGREDIENTS: DEXTROMETHORPHAN HYDROBROMIDE 10 mg/5 mL; BROMPHENIRAMINE MALEATE 10 mg/5 mL; PHENYLEPHRINE HYDROCHLORIDE 10 mg/5 mL
INACTIVE INGREDIENTS: SUCRALOSE; CAULOPHYLLUM THALICTROIDES ROOT; ECHINACEA, UNSPECIFIED; EUCALYPTUS GLOBULUS LEAF; GINKGO; GOLDENSEAL; HONEY; GLYCYRRHIZA GLABRA; MENTHOL; METHYLPARABEN; VERBASCUM DENSIFLORUM LEAF; MYRRH; POTASSIUM CITRATE; POTASSIUM SORBATE; PROPYLENE GLYCOL; PROPYLPARABEN; WATER; ULMUS RUBRA BARK; SODIUM CHLORIDE; PRUNUS SEROTINA BARK; ZINC SULFATE; HOREHOUND; CITRIC ACID MONOHYDRATE; POLYGLYCERIN-10

Drug Facts

Active ingredients (in each 5 mls tsp.) Purpose
Dextromethorphan HBr 10 mg ........................... Cough Suppressant
Brompheniramine Maleate 4 mg ................................. Antihistaminic
Phenylephrine HCl 10 mg ................................. Nasal Decongestant

Purpose

Antihistamine

Cough Suppressant

Nasal Decongestant

USES

- temporarily relieves runny nose, sneezing, itching of the nose or throat and itchy watery eyes due to hay fever or other upper respiratory allergies
- temporarily relieves cough and nasal congestion as may occur with the common cold

Warnings

Do not exceed recommended dosage

Do not use • If you are taking a prescription monoamine oxidase inhibitor (MAOI) (certain drugs for depression, psychiatric, or emotional conditions or Parkinson’s disease), or for 2 weeks after stopping the MAOI drug. If you do not know if you are taking a prescription drug that contains an MAOI; ask your doctor or pharmacist before taking this product.

Ask a doctor before use if you have • heart disease • glaucoma • high blood pressure • thyroid disease • diabetes • difficulty in urination due to an enlarged prostate gland • a persistent or chronic cough such as occurs with smoking, asthma or emphysema • a cough that is accompanied by excessive phlegm (mucus) • a breathing problem such as emphysema or chronic bronchitis
Ask a doctor or pharmacist before use if you are taking sedatives
or tranquilizers.

When using this product • may cause drowsiness • avoid alcoholic drinks • alcohol, sedatives, and tranquilizers may increase drowsiness • be careful when driving a motor vehicle or operating machinery • excitability may occur, especially in children.

Stop use and ask a doctor if • symptoms do not improve within 7 days, cough tends to recur, or symptoms are accompanied by a fever, rash or persistent headache. A persistent cough may be a sign of a serious condition. • if nervousness, dizziness, or sleeplessness occur

PREGNANCY OR BREAST FEEDING

If pregnant or breast-feeding, ask a health professional before use.

Keep out of reach of children.

In case of overdose, get medical help or contact a Poison Control Center right away.

Directions:

- shake well before use
- do not exceed more than 6 doses in any 24-hour period or as directed by a doctor

Age Dose

adults and children 12 years of age and over 5 mL (1 tsp) every 4 hours

children 6 to under 12 years of age 2.5 mL (1/2 tsp) every 4 hours

children under 6 years of age consult a doctor

Inactive Ingredients:

Blue Cohosh root extract, Citric Acid, Echinacea root extract, Eucalyptus Oil, Ginkgo Biloba leaf extract, Glycerine, Golden Seal Root extract,
Honey Flavor, Horehound, Licorice Root extract, Menthol, Methylparaben, Mullein Leaf extract, Myrrh gum extract, Potassium Citrate,
Potassium Sorbate, Propylene Glycol, Propylparaben, Slippery Elm Bark extract, Sodium Chloride, Sucralose, Water, Wild Cherry Bark extract, Zinc Sulfate.

Questions or Comments?

305-805-3456 Monday - Friday 9AM to 5PM EST

www.efficientlabs.com